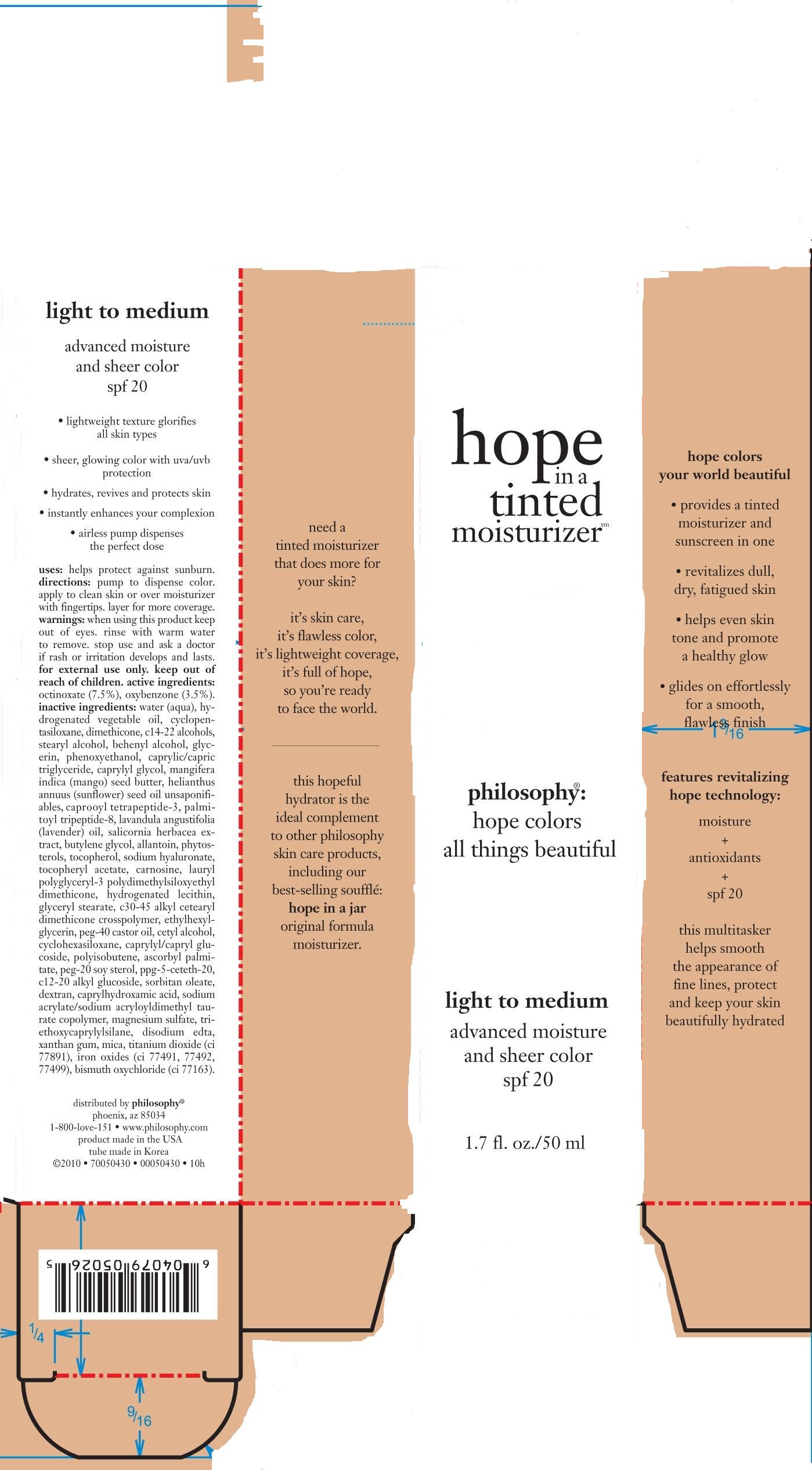 DRUG LABEL: Hope In A Tinted Moisturizer
NDC: 50184-6300 | Form: CREAM
Manufacturer: Philosophy, Inc.
Category: otc | Type: HUMAN OTC DRUG LABEL
Date: 20100825

ACTIVE INGREDIENTS: OCTINOXATE 3.75 mL/50 mL; OXYBENZONE 1.75 mL/50 mL
INACTIVE INGREDIENTS: WATER; CYCLOMETHICONE 5; DIMETHICONE; STEARYL ALCOHOL; DOCOSANOL; GLYCERIN; PHENOXYETHANOL; MEDIUM-CHAIN TRIGLYCERIDES; CAPRYLYL GLYCOL; MANGO; SUNFLOWER OIL; ENGLISH LAVENDER OIL; BUTYLENE GLYCOL; ALLANTOIN; .BETA.-SITOSTEROL; ALPHA-TOCOPHEROL; HYALURONATE SODIUM; .ALPHA.-TOCOPHEROL ACETATE, D-; CARNOSINE; HYDROGENATED SOYBEAN LECITHIN; GLYCERYL MONOSTEARATE; ETHYLHEXYLGLYCERIN; POLYOXYL 40 CASTOR OIL; CETYL ALCOHOL; CYCLOMETHICONE 6; ASCORBYL PALMITATE; PPG-5-CETETH-20; SORBITAN MONOOLEATE; DEXTRAN 1; CAPRYLHYDROXAMIC ACID; MAGNESIUM SULFATE, UNSPECIFIED; OCTYLTRIETHOXYSILANE; EDETATE DISODIUM; XANTHAN GUM; MICA; TITANIUM DIOXIDE; FERRIC OXIDE RED; FERRIC OXIDE YELLOW; FERROSOFERRIC OXIDE; BISMUTH OXYCHLORIDE

Drug Facts

ACTIVE INGREDIENTS:

OCTINOXATE (7.5%)

OXYBENXONE (3.5%)

INACTIVE INGREDIENTS:

WATER/AQUA/EAU

HYDROGENATED VEGETABLE OIL

CYCLOPENTASILOXANE

DIMETHICONE

C14-22 ALCOHOLS

STEARYL ALCOHOL

BEHENYL ALCOHOL

GLYCERIN

PHENOXYETHNOL

CAPRYLIC/CAPRIC TRIGLYCERIDES

CAPRYLYL GLYCOL

MANGIFERA INDICA (MANGO) SEED OIL UNSAPONIFIABLES

HELIANTHUS ANNUUS (SUNFLOWER) SEED OIL UNSAPONIFIABLES

CAPROOYL TETRAPEPTIDE-3

PALMITOYL TRIPEPTIDE-8

LAVANDULA ANGUSTIFOLIA (LAVENDER) OIL

SALICORNIA HERBACEA EXTRACT

BUTYLENE GLYCOL

ALLANTOIN

PHYTOSTEROLS

TOCOPHEROL

SODIUM HYALURONATE

TOCOPHERYL ACETATE

CARNOSINE

LAURYL POLYGLYCERYL-3 POLYDIMETHYLSILOXYETHYL DIMETHICONE

HYDROGENATED LECITHIN

GLYCERYL STEARATE

C30-45 ALKYL CETEARYL DIMETHICONE CROSSPOLYMER

ETHYLHEXYLGLYCERIN

PEG-40 CASTOR OIL

CETYL ALCOHOL

CYCLOHEXASILOXANE

CAPRYLYL/CAPRYL GLUCOSIDE

POLYISOBUTENE

ASCROBYL PALMITATE

PEG-20 SOY STEROL

c12-20 ALKYL GLUCOSIDE

SORBITAN OLEATE

DEXTRAN

CAPRYLHYDROXAMIC ACID

SODIUM ACRYLATE/SODIUM ACRYLOYLDIMETHYL TAURATE COPLOYMER

MAGNESIUM SULFATE

TRIETHOXYCAPRYLYLSILANE

DISODIUM EDTA

XANTHAN GUM

MICA

TITANIUM DIOXIDE (CI 77891)

IRON OXIDES (CI 77491, 77492, 77499)

BISMUTH OXYCHLORIDE (CI 77163)

PURPOSE

HELPS PROTECT AGAINST SUNBURN.

FOR EXTERNAL USE ONLY

WHEN USING THIS PRODUCT KEEP OUT OF EYES. RINSE WITH WARM WATER TO REMOVE.

ASK A DOCTOR IF A RASH OR IRRITATION DEVELOPS AND LASTS.

KEEP OUT OF REACH OF CHILDREN.

PACKAGE LABEL

Enter section text here